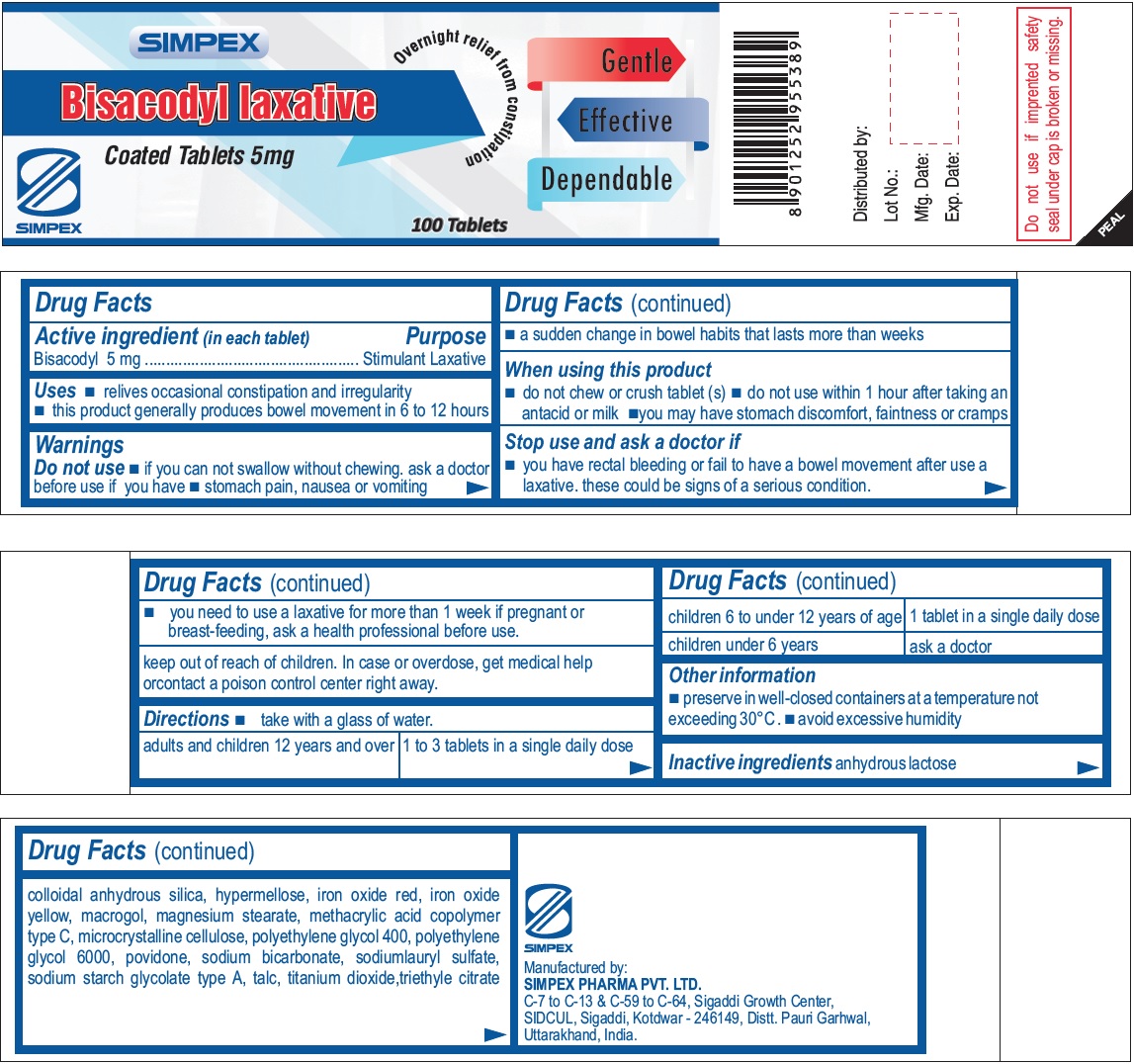 DRUG LABEL: SIMPEX Bisacodyl laxative
NDC: 76457-003 | Form: TABLET, COATED
Manufacturer: Simpex Pharma Pvt. Ltd
Category: otc | Type: HUMAN OTC DRUG LABEL
Date: 20231129

ACTIVE INGREDIENTS: BISACODYL 5 mg/1 1
INACTIVE INGREDIENTS: ANHYDROUS LACTOSE; SILICON DIOXIDE; HYPROMELLOSE 2208 (15000 MPA.S); FERRIC OXIDE RED; FERRIC OXIDE YELLOW; POLYETHYLENE GLYCOL, UNSPECIFIED; MAGNESIUM STEARATE; METHACRYLIC ACID - ETHYL ACRYLATE COPOLYMER (1:1) TYPE A; MICROCRYSTALLINE CELLULOSE; POLYETHYLENE GLYCOL 400; POLYETHYLENE GLYCOL 600; POVIDONE; SODIUM BICARBONATE; SODIUM LAURYL SULFATE; TALC; TITANIUM DIOXIDE; TRIETHYL CITRATE

SIMPEX Bisacodyl laxative

Active ingredient (in each tablet)

Bisacodyl 5 mg

Purpose

Stimulant Laxative

Uses

- relives occasional constipation and irregularity
- this product generally produces bowel movement in 6 to 12 hours

Warnings

Do not use

- if you can not swallow without chewing. ask a doctor before use if you have
- stomach pain, nausea or vomiting
- a sudden change in bowel habits that lasts more than weeks

When using this product

- do not chew or crush tablet (s)
- do not use within 1 hour after taking an antacid or milk
- you may have stomach discomfort, faintness or cramps

Stop use and ask a doctor if

- you have rectal bleeding or fail to have a bowel movement after use a laxative. these could be signs of a serious condition.
- you need to use a laxative for more than 1 week if pregnant or breast-feeding, ask a health professional before use.

keep out of reach of children.

In case or overdose, get medical help orcontact a poison control center right away.

Directions

- take with a glass of water.

Adults and children 12 years and over | take 1 to 3 tablets in a single daily dose
Children 6 to under 12 years of age | take 1 tablet in a single daily dose
Children under 6 years | ask a doctor

Other information

- preserve in well-closed containers at a temperature not exceeding 30°C
- avoid excessive humidity

Inactive ingredients

anhydrous lactose, colloidal anhydrous silica, hypermellose, iron oxide red, iron oxide yellow, macrogol, magnesium stearate, methacrylic acid copolymer type C, microcrystalline cellulose, polyethylene glycol 400, polyethylene glycol 6000, povidone, sodium bicarbonate, sodiumlauryl sulfate, sodium starch glycolate type A, talc, titanium dioxide,triethyle citrate